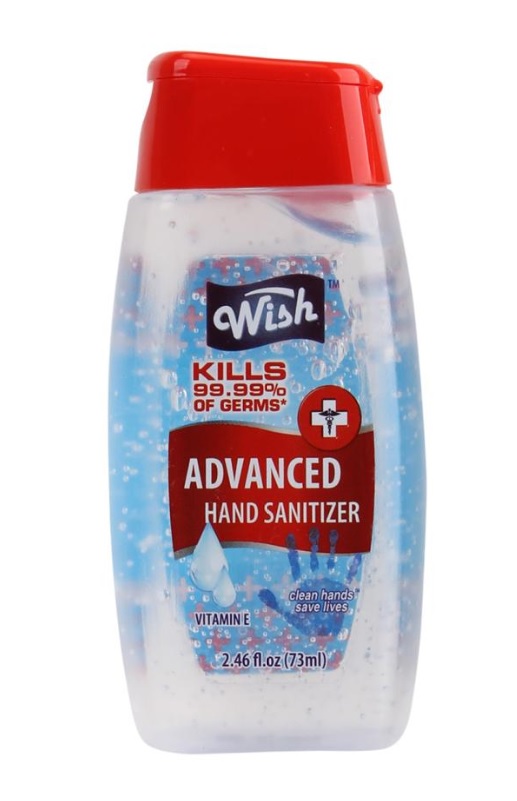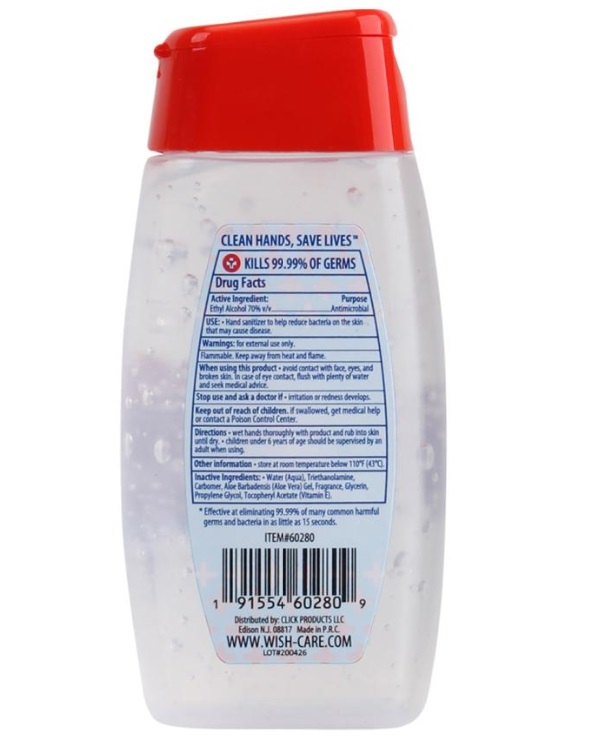 DRUG LABEL: Wish advanced hand sanitizer
NDC: 71611-100 | Form: GEL
Manufacturer: Click Products LLC
Category: otc | Type: HUMAN OTC DRUG LABEL
Date: 20201210

ACTIVE INGREDIENTS: ALCOHOL 70.4 mL/100 mL
INACTIVE INGREDIENTS: CARBOMER 940 0.3 mL/100 mL; GLYCERIN 0.5 mL/100 mL; PROPYLENE GLYCOL 0.5 mL/100 mL; TROLAMINE 0.3 mL/100 mL; .ALPHA.-TOCOPHEROL ACETATE 0.05 mL/100 mL; ALOE VERA LEAF 0.05 mL/100 mL; WATER 27.7 mL/100 mL; ALOE 0.2 mL/100 mL

Advanced wish hand sanitizer- Vit E

Hand Sanitizer

Kills 99.9% of germs

Active ingredient

Active Ingredient Purpose

Ethyl Alcohol 70% v/v Antimicrobial

use

Reduce bacteria and viruses onthe hands that may cause disease.

Warning

for external use only.

Flammable

Keep away from heat and flame.

When using this product

Avoid contact with face, eyes and broken skin. In case of eye contact, flush with plenty of water and seek medical advice.

Stop and ask a doctor if

irritation or redness develops.

Keep out of reach of children.

If swallowed get immediate medical help or contact a poison contaol center right away.

Directions

DOSAGE AND ADMINISTRATION

Wet hands thoroughly with product and rub into skin until dry.

USER SAFETY WARNINGS

Children under 6 years of age should be supervised by an adult when using.

Inactive Ingredients:

Water(aqua), Glycerin, Propylene Glycol, Carbomer, Triethanolamine, Fragrance, Aloe Barbadensis(Aloe Vera) Gel, Tocopheryl acetate(vitamin E).